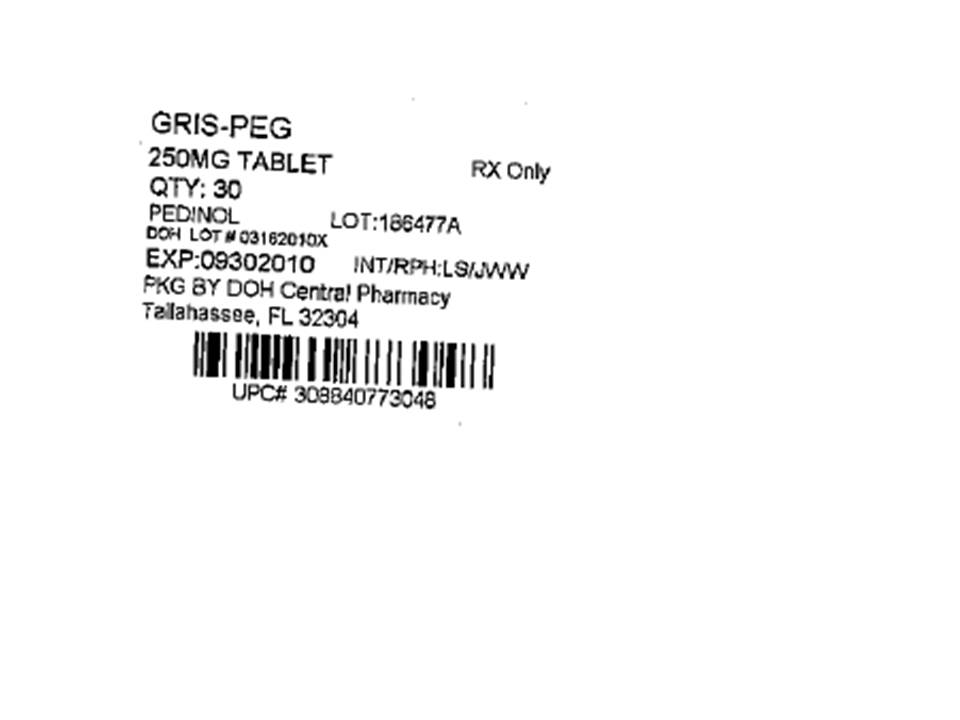 DRUG LABEL: Gris-PEG
NDC: 53808-0261 | Form: TABLET, FILM COATED
Manufacturer: State of Florida DOH Central Pharmacy
Category: prescription | Type: HUMAN PRESCRIPTION DRUG LABEL
Date: 20100601

ACTIVE INGREDIENTS: GRISEOFULVIN 250 mg/1 1
INACTIVE INGREDIENTS: SILICON DIOXIDE; MAGNESIUM STEARATE; METHYLPARABEN; POLYETHYLENE GLYCOL 800; POVIDONE; SODIUM LAURYL SULFATE; TITANIUM DIOXIDE; POLYETHYLENE GLYCOL 8000

Gris-PEG®
(griseofulvin ultramicrosize)
Tablets, USP
125 mg; 250 mg

DESCRIPTION

Gris-PEG® Tablets contain ultramicrosize crystals of griseofulvin, an antibiotic derived from a species of Penicillium.

Each Gris-PEG® tablet contains:

Active Ingredient: griseofulvin ultramicrosize .... 125 mg

Inactive Ingredients: colloidal silicon dioxide, lactose, magnesium stearate, methylcellulose, methylparaben, polyethylene glycol 400 and 8000, polyvinylpyrrolidone, and titanium dioxide.

or

Active Ingredient: griseofulvin ultramicrosize .... 250 mg

Inactive Ingredients: colloidal silicon dioxide, magnesium stearate, methylcellulose, methylparaben, polyethylene glycol 400 and 8000, povidone, sodium lauryl sulfate, and titanium dioxide.

ACTION

Microbiology

Griseofulvin is fungistatic with in vitro activity against various species of Microsporum, Epidermophyton and Trichophyton. It has no effect on bacteria or other genera of fungi.

Pharmacokinetics

Following oral administration, griseofulvin is deposited in the keratin precursor cells and has a greater affinity for diseased tissue. The drug is tightly bound to the new keratin which becomes highly resistant to fungal invasions.

The efficiency of gastrointestinal absorption of ultramicrocrystalline griseofulvin is approximately one and one-half times that of the conventional microsize griseofulvin. This factor permits the oral intake of two-thirds as much ultramicrocrystalline griseofulvin as the microsize form. However, there is currently no evidence that this lower dose confers any significant clinical differences with regard to safety and/or efficacy.

In a bioequivalence study conducted in healthy volunteers (N=24) in the fasted state, 250 mg ultramicrocrystalline griseofulvin tablets were compared with 250 mg ultramicrocrystalline griseofulvin tablets that were physically altered (crushed) and administered with applesauce. The 250 mg ultramicrocrystalline griseofulvin tablets were found to be bioequivalent to the physically altered (crushed) 250 mg ultramicrocrystalline griseofulvin tablets (See Table 1).

Table 1: Mean (± SD) of the Pharmacokinetic Parameters for Griseofulvin administered in applesauce as a Single Dose of Gris-PEG® 250-mg Tablets Uncrushed and Crushed to fasted Healthy Volunteers (N=24)
 | 250 mg Ultramicrocrystalline Griseofulvin Tablets Unaltered | 250 mg Ultramicrocrystalline Griseofulvin Tablets Physically Altered (Crushed and in Applesauce)
Cmax (ng/mL) | 600.61 (± 167.6) | 672.61 (± 146.2)
Tmax (hr) | 4.04 (± 2.2) | 3.08 (± 1.02)
AUC (ng.hr/mL) | 8618.89 (± 1907.2) | 9023.71 (± 1911.5)

INDICATIONS

Gris-PEG® (griseofulvin ultramicrosize) is indicated for the treatment of the following ringworm infections; tinea corporis (ringworm of the body), tinea pedis (athlete's foot), tinea cruris (ringworm of the groin and thigh), tinea barbae (barber's itch), tinea capitis (ringworm of the scalp), and tinea unguium (onychomycosis, ringworm of the nails), when caused by one or more of the following genera of fungi: Trichophyton rubrum, Trichophyton tonsurans, Trichophyton mentagrophytes, Trichophyton interdigitalis,Trichophyton verrucosum, Trichophyton megnini, Trichophyton gallinae, Trichophyton crateriform, Trichophyton sulphureum, Trichophyton schoenleini, Microsporum audouini, Microsporum canis, Microsporum gypseum and Epidermophyton floccosum. NOTE: Prior to therapy, the type of fungi responsible for the infection should be identified. The use of the drug is not justified in minor or trivial infections which will respond to topical agents alone. Griseofulvin is not effective in the following: bacterial infections, candidiasis (moniliasis), histoplasmosis, actinomycosis, sporotrichosis, chromoblastomycosis, coccidioidomycosis, North American blastomycosis, cryptococcosis (torulosis), tinea versicolor and nocardiosis.

CONTRAINDICATIONS

Two cases of conjoined twins have been reported since 1977 in patients taking griseofulvin during the first trimester of pregnancy. Griseofulvin should not be prescribed to pregnant patients. If the patient becomes pregnant while taking this drug, the patient should be apprised of the potential hazard to the fetus.

This drug is contraindicated in patients with porphyria or hepatocellular failure and in individuals with a history of hypersensitivity to griseofulvin.

WARNINGS

Prophylactic Usage

Safety and efficacy of griseofulvin for prophylaxis of fungal infections have not been established.

Animal Toxicology

Chronic feeding of griseofulvin, at levels ranging from 0.5%-2.5% of the diet resulted in the development of liver tumors in several strains of mice, particularly in males. Smaller particle sizes result in an enhanced effect. Lower oral dosage levels have not been tested. Subcutaneous administration of relatively small doses of griseofulvin once a week during the first three weeks of life has also been reported to induce hepatomata in mice. Thyroid tumors, mostly adenomas but some carcinomas, have been reported in male rats receiving griseofulvin at levels of 2.0%, 1.0% and 0.2% of the diet, and in female rats receiving the two higher dose levels. Although studies in other animal species have not yielded evidence of tumorigenicity, these studies were not of adequate design to form a basis for conclusion in this regard. In subacute toxicity studies, orally administered griseofulvin produced hepatocellular necrosis in mice, but this has not been seen in other species. Disturbances in porphyrin metabolism have been reported in griseofulvin-treated laboratory animals. Griseofulvin has been reported to have a colchicine-like effect on mitosis and cocarcinogenicity with methylcholanthrene in cutaneous tumor induction in laboratory animals.

Usage in Pregnancy

See CONTRAINDICATIONS section.

Animal Reproduction Studies

It has been reported in the literature that griseofulvin was found to be embryotoxic and teratogenic on oral administration to pregnant rats. Pups with abnormalities have been reported in the litters of a few bitches treated with griseofulvin. Suppression of spermatogenesis has been reported to occur in rats, but investigation in man failed to confirm this.

PRECAUTIONS

Patients on prolonged therapy with any potent medication should be under close observation. Periodic monitoring of organ system function, including renal, hepatic and hematopoietic, should be done. Since griseofulvin is derived from species of Penicillium, the possibility of cross-sensitivity with penicillin exists; however, known penicillin-sensitive patients have been treated without difficulty. Since a photosensitivity reaction is occasionally associated with griseofulvin therapy, patients should be warned to avoid exposure to intense natural or artificial sunlight. Lupus erythematosus or lupus-like syndromes have been reported in patients receiving griseofulvin. Griseofulvin decreases the activity of warfarin-type anticoagulants so that patients receiving these drugs concomitantly may require dosage adjustment of the anticoagulant during and after griseofulvin therapy. Barbiturates usually depress griseofulvin activity and concomitant administration may require a dosage adjustment of the antifungal agent. There have been reports in the literature of possible interactions between griseofulvin and oral contraceptives. The effect of alcohol may be potentiated by griseofulvin, producing such effects as tachycardia and flush.

ADVERSE REACTIONS

When adverse reactions occur, they are most commonly of the hypersensitivity type such as skin rashes, urticaria, erythema multiform-like drug reactions, and rarely, angioneurotic edema, and may necessitate withdrawal of therapy and appropriate countermeasures. Paresthesia of the hands and feet have been reported rarely after extended therapy. Other side effects reported occasionally are oral thrush, nausea, vomiting, epigastric distress, diarrhea, headache, fatigue, dizziness, insomnia, mental confusion, and impairment of performance of routine activities. Proteinuria and leukopenia have been reported rarely. Administration of the drug should be discontinued if granulocytopenia occurs. When rare, serious reactions occur with griseofulvin, they are usually associated with high dosages, long periods of therapy, or both.

DOSAGE AND ADMINISTRATION

Accurate diagnosis of infecting organism is essential. Identification should be made either by direct microscopic examination of a mounting of infected tissue in a solution of potassium hydroxide or by culture on an appropriate medium. Medication must be continued until the infecting organism is completely eradicated as indicated by appropriate clinical or laboratory examination. Representative treatment periods are tinea capitis, 4 to 6 weeks; tinea corporis, 2 to 4 weeks; tinea pedis, 4 to 8 weeks; tinea unguium-depending on rate of growth-fingernails, at least 4 months; toenails, at least 6 months.

General measures in regard to hygiene should be observed to control sources of infection or reinfection. Concomitant use of appropriate topical agents is usually required, particularly in treatment of tinea pedis. In some forms of athlete's foot, yeasts and bacteria may be involved as well as fungi. Griseofulvin will not eradicate the bacterial or monilial infection.

Gris-PEG® tablets may be swallowed whole or crushed and sprinkled onto 1 tablespoonful of applesauce and swallowed immediately without chewing.

Adults

Daily administration of 375 mg (as a single dose or in divided doses) will give a satisfactory response in most patients with tinea corporis, tinea cruris, and tinea capitis. For those fungal infections more difficult to eradicate, such as tinea pedis and tinea unguium, a divided dose of 750 mg is recommended.

Pediatric Use

Approximately 3.3 mg per pound of body weight per day of ultramicrosize griseofulvin is an effective dose for most pediatric patients. On this basis, the following dosage schedule is suggested: Children weighing 35-60 pounds - 125 mg to 187.5 mg daily. Pediatric patients weighing over 60 pounds - 187.5 mg to 375 mg daily. Children and infants 2 years of age and younger - dosage has not been established.

Clinical experience with griseofulvin in children with tinea capitis indicates that a single daily dose is effective. Clinical relapse will occur if the medication is not continued until the infecting organism is eradicated.

HOW SUPPLIED

Gris-PEG® (griseofulvin ultramicrosize) Tablets, 125 mg, white scored, elliptical-shaped, embossed "Gris-PEG" on one side and "125" on the other. Gris-PEG® (griseofulvin ultramicrosize) Tablets, 250 mg, white scored, capsule-shaped, embossed "Gris-PEG" on one side and "250" on the other. Both strengths are film-coated.

They are supplied by State of Florida DOH Central Pharmacy as follows:

NDC | Strength | Quantity/Form | Color | Source Prod. Code
53808-0261-1 | 250 mg | 30 Tablets in a Blister Pack | white | 0884-0773

Rx ONLY

STORAGE

Store Gris-PEG ® tablets at controlled room temperature 15° - 30°C (59° - 86°F) in tight, light-resistant containers.

Manufactured for:
PEDINOL PHARMACAL INC.
Farmingdale, NY 11735 U.S.A.
By:
NOVARTIS CONSUMER HEALTH INC.
Lincoln, NE 68501

This Product was Repackaged By:

State of Florida DOH Central Pharmacy
104-2 Hamilton Park Drive
Tallahassee, FL 32304
United States